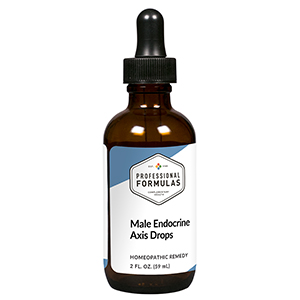 DRUG LABEL: Male Endocrine Axis Drops
NDC: 63083-5019 | Form: LIQUID
Manufacturer: Professional Complementary Health Formulas
Category: homeopathic | Type: HUMAN OTC DRUG LABEL
Date: 20190815

ACTIVE INGREDIENTS: POPULUS TREMULOIDES BARK 1 [hp_X]/59 mL; SAW PALMETTO 1 [hp_X]/59 mL; SOLIDAGO VIRGAUREA FLOWERING TOP 2 [hp_X]/59 mL; PYGEUM 3 [hp_X]/59 mL; SMILAX ORNATA ROOT 3 [hp_X]/59 mL; ZINC 3 [hp_X]/59 mL; TURNERA DIFFUSA LEAFY TWIG 4 [hp_X]/59 mL; SUS SCROFA ADRENAL GLAND 6 [hp_X]/59 mL; FERRIC CATION 6 [hp_X]/59 mL; BOS TAURUS TESTICLE 6 [hp_X]/59 mL; BOS TAURUS PITUITARY GLAND, POSTERIOR 6 [hp_X]/59 mL; BOS TAURUS PROSTATE GLAND 6 [hp_X]/59 mL; SELENIUM 6 [hp_X]/59 mL
INACTIVE INGREDIENTS: ALCOHOL; WATER

HMEA

ACTIVE INGREDIENTS

Populus tremuloides 1X
Sabal serrulata 1X
Solidago virgaurea 2X
Pygeum africanum 3X
Sarsaparilla 3X
Zincum metallicum 3X
Damiana 4X
Adrenal 6X
Ferrum picricum 6X
Orchic 6X
Pituitary 6X
Prostate 6X
Selenium metallicum 6X

QUESTIONS

Professional Formulas

PO Box 2034 Lake Oswego, OR 97035

INDICATIONS

For the temporary relief of diminished sexual desire or performance, muscle weakness or decreased strength, sleep disturbances, weight gain, frequent or difficult urination, or fatigue.*

PURPOSE

*Claims based on traditional homeopathic practice, not accepted medical evidence. Not FDA evaluated.

WARNINGS

Consult a doctor if condition worsens or if symptoms persist. Keep out of the reach of children. In case of overdose, get medical help or contact a poison control center right away. If pregnant or breastfeeding, ask a healthcare professional before use.

Keep out of the reach of children.

PREGNANCY OR BREAST FEEDING

If pregnant or breastfeeding, ask a healthcare professional before use.

DIRECTIONS

Place drops under tongue 30 minutes before/after meals. Adults and children 12 years and over: Take 10 drops up to 3 times per day. Consult a physician for use in children under 12 years of age.

OTHER INFORMATION

Tamper resistant. If seal is broken, do not use. After opening, close container tightly and store at room temperature away from heat.

INACTIVE INGREDIENTS

20% ethanol, purified water.

LABEL

Est 1985

Professional Formulas

Complementary Health

Male Endocrine Axis Drops

Homeopathic Remedy

2 FL. OZ. (59 mL)